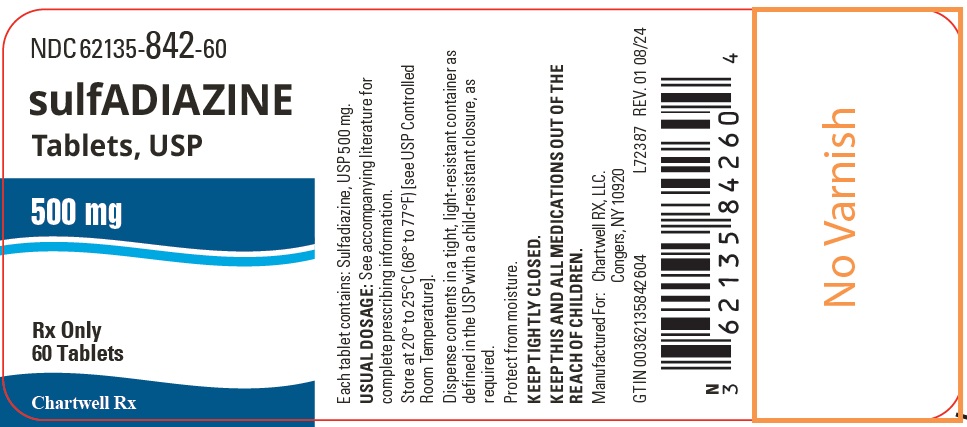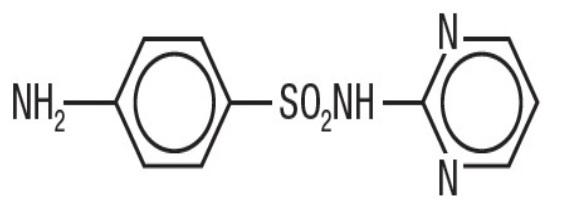 DRUG LABEL: sulfADIAZINE
NDC: 62135-842 | Form: TABLET
Manufacturer: Chartwell RX, LLC
Category: prescription | Type: HUMAN PRESCRIPTION DRUG LABEL
Date: 20240924

ACTIVE INGREDIENTS: SULFADIAZINE 500 mg/1 1
INACTIVE INGREDIENTS: SILICON DIOXIDE; STARCH, CORN; CROSCARMELLOSE SODIUM; CALCIUM STEARATE; SUCROSE; LACTOSE MONOHYDRATE

sulfADIAZINE TABLETS, USP

DESCRIPTION

Sulfadiazine is an oral sulfonamide antibacterial agent.

Sulfadiazine Tablets, USP contains 500 mg Sulfadiazine, USP. Inactive ingredients: corn starch, colloidal silicon dioxide, croscarmellose sodium, calcium stearate, lactose monohydrate, and sucrose.

Sulfadiazine, USP occurs as a white or slightly yellow powder. It is odorless or nearly so and slowly darkens on exposure to light. It is practically insoluble in water and slightly soluble in alcohol. The chemical name of sulfadiazine is N^1-2-pyrimidinylsulfanilamide. The empirical formula is C10H10N4O2S. It has a molecular weight of 250.28. The pH ranges between 5.5 and 7.5. The structural is shown below:

C10H10N4O2S M.W. 250.28

Sulfadiazine

Most sulfonamides slowly darken on exposure to light.

CLINICAL PHARMACOLOGY

The systemic sulfonamides are bacteriostatic agents having a similar spectrum of activity. Sulfonamides competitively inhibit bacterial synthesis of folic acid (pteroylglutamic acid) from aminobenzoic acid. Resistant strains are capable of utilizing folic acid precursors or preformed folic acid.

Sulfonamides exist in the blood in 3 forms – free, conjugated (acetylated and possibly others) and protein bound. The free form is considered to be the therapeutically active one.

Sulfadiazine given orally is readily absorbed from the gastrointestinal tract. After a single 2 g oral dose, a peak of 6.04 mg/100 mL is reached in 4 hours; of this, 4.65 mg/100 mL is free drug.

When a dose of 100 mg/kg of body weight is given initially and followed by 50 mg/kg every 6 hours, blood levels of free sulfadiazine are about 7 mg/100mL. Protein binding is 38% to 48%. Sulfadiazine diffuses into the cerebrospinal fluid; free drug reaches 32% to 65% of blood levels and total drug 40% to 60%.

Sulfadiazine is excreted largely in the urine, where concentrations are 10 to 25 times greater than serum levels. Approximately 10% of a single oral dose is excreted in the first 6 hours, 50% within 24 hours and 60% to 85% in 48 to 72 hours. Of the amount excreted in the urine, 15% to 40% is in the acetyl form.

INDICATIONS AND USAGE

Sulfadiazine Tablets are indicated in the following conditions:

Chancroid

Trachoma

Inclusion conjunctivitis

Nocardiosis

Urinary tract infections (primarily pyelonephritis, pyelitis and cystitis) in the absence of obstructive uropathy or foreign bodies, when these infections are caused by susceptible strains of the following organisms: Escherichia coli, Klebsiella species, Enterobacter species, Staphylococcus aureus, Proteus mirabilisand P. vulgaris. Sulfadiazine should be used for urinary tract infections only after use of more soluble sulfonamides has been unsuccessful.

Toxoplasmosis encephalitis in patients with and without acquired immunodeficiency syndrome, as adjunctive therapy with pyrimethamine.

Malaria due to chloroquine-resistant strains of Plasmodium falciparum, when used as adjunctive therapy.

Prophylaxis of meningococcal meningitis when sulfonamide-sensitive group A strains are known to prevail in family groups or larger closed populations (the prophylactic usefulness of sulfonamides when group B or C infections are prevalent is not proved and may be harmful in closed population groups).

Meningococcal meningitis, when the organism has been demonstrated to be susceptible.

Acute otitis media due to Haemophilus influenzae, when used concomitantly with adequate doses of penicillin.

Prophylaxis against recurrences of rheumatic fever, as an alternative to penicillin.

H. influenzaemeningitis, as adjunctive therapy with parental streptomycin.

IMPORTANT NOTES

In vitrosulfonamide susceptibility tests are not always reliable. The test must be carefully coordinated with bacteriologic and clinical response. When the patient is already taking sulfonamides, follow-up cultures should have aminobenzoic acid added to the culture media.

Currently, the increasing frequency of resistant organisms limits the usefulness of antibacterial agents, including the sulfonamides, especially in the treatment of recurrent and complicated urinary tract infections.

Wide variation in blood levels may result with identical doses. Blood levels should be measured in patients receiving sulfonamides for serious infections. Free sulfonamide blood levels of 5 mg to 15 mg per 100 mL may be considered therapeutically effective for most infections and blood levels of 12 mg to 15 mg per 100 mL may be considered optimal for serious infections. Twenty mg per 100 mL should be the maximum total sulfonamide level, since adverse reactions occur more frequently above this level.

CONTRAINDICATIONS

Sulfadiazine is contraindicated in the following circumstances: Hypersensitivity to sulfonamides.

In infants less than 2 months of age (except as adjunctive therapy with pyrimethamine in the treatment of congenital toxoplasmosis).

In pregnancy at term and during the nursing period, because sulfonamides cross the placenta and are excreted in breast milk and may cause kernicterus.

WARNINGS

The sulfonamides should notbe used for the treatmentof group A betahemolytic streptococcal infections. In an established infection, they will not eradicate the streptococcus and, therefore, will not prevent sequelae such as rheumatic fever and glomerulonephritis.

Deaths associated with the administration of sulfonamides have been reported from hypersensitivity reactions, agranulocytosis, aplastic anemia and other blood dyscrasias.

The presence of such clinical signs as sore throat, fever, pallor, purpura or jaundice may be early indications of serious blood disorders.

The frequency of renal complications is considerably lower in patients receiving the more soluble sulfonamides.

PRECAUTIONS

General

Sulfonamides should be given with caution to patients with impaired renal or hepatic function and to those with severe allergy or bronchial asthma.

Hemolysis may occur in individuals deficient in glucose-6-phosphate dehydrogenase. This reaction is dose related.

Adequate fluid intake must be maintained in order to prevent crystalluria and stone formation.

Information for Patients

Patients should be instructed to drink an eight ounce glass of water with each dose of medication and at frequent intervals throughout the day. Caution patients to report promptly the onset of sore throat, fever, pallor, purpura or jaundice when taking this drug, since these may be early indications of serious blood disorders.

Laboratory Tests

Complete blood counts and urinalyses with careful microscopic examinations should be done frequently in patients receiving sulfonamides.

Drug Interactions

Administration of a sulfonamide may increase the effect of oral anticoagulants and methotrexate, probably by displacement of these drugs from binding sites on plasma albumin. Potentiation of the action of sulfonylurea hypoglycemic agents, thiazide diuretics and uricosuric agents may also be noted. This may also be due to displacement of the drugs from albumin or a pharmacodynamic mechanism may play a role. Conversely, agents such as indomethacin, probenecid and salicylates may displace sulfonamides from plasma albumin and increase the concentrations of free drug in plasma.

Carcinogenesis, Mutagenesis, Impairment of Fertility

The sulfonamides bear certain chemical similarities to some goitrogens. Rats appear to be especially susceptible to the goitrogenic effects of sulfonamides and long-term administration has produced thyroid malignancies in rats.

Pregnancy

Teratogenic Effects

The safe use of sulfonamides in pregnancy has not been established. The teratogenic potential of most sulfonamides has not been thoroughly investigated in either animals or humans. However, a significant increase in the incidence of cleft palate and other bony abnormalities in offspring has been observed when certain sulfonamides of the short, intermediate and long acting types were given to pregnant rats and mice in high oral doses (7 to 25 times the human therapeutic dose).

Nursing Mothers

Sulfadiazine is contraindicated for use in nursing mothers because the sulfonamides cross the placenta, are excreted in breast milk and may cause kernicterus.

Because of the potential for serious adverse reactions in nursing infants from sulfadiazine, a decision should be made whether to discontinue nursing or to discontinue the drug, taking into account the importance of the drug to the mother. See CONTRAINDICATIONS.

Pediatric Use

Sulfadiazine is contraindicated in infants less than 2 months of age (except as adjunctive therapy with pyrimethamine in the treatment of congenital toxoplasmosis). See CONTRAINDICATIONSand DOSAGE AND ADMINISTRATION.

ADVERSE REACTIONS

Blood Dyscrasias

Agranulocytosis, aplastic anemia, thrombocytopenia, leukopenia, hemolytic anemia, purpura, hypoprothrombinemia and methemoglobinemia.

Allergic Reactions

Erythema multiforme (Stevens-Johnson syndrome), generalized skin eruptions, epidermal necrolysis, urticaria, serum sickness, pruritus, exfoliative dermatitis, anaphylactoid reactions, periorbital edema, conjunctival and scleral injection, photosensitization, arthralgia, allergic myocarditis, drug fever and chills.

Gastrointestinal Reactions

Nausea, emesis, abdominal pains, hepatitis, diarrhea, anorexia, pancreatitis and stomatitis.

C.N.S. Reactions

Headache, peripheral neuritis, mental depression, convulsions, ataxia, hallucinations, tinnitus, vertigo and insomnia.

Renal

Crystalluria, stone formation, toxic nephrosis with oliguria and anuria; periarteritis nodosa and lupus erythematosus phenomenon have been noted.

Miscellaneous Reactions

The sulfonamides bear certain chemical similarities to some goitrogens, diuretics (acetazolamide and the thiazides) and oral hypoglycemic agents. Goiter production, diuresis and hypoglycemia have occurred rarely in patients receiving sulfonamides. Cross-sensitivity may exist with these agents.

DOSAGE AND ADMINISTRATION

SYSTEMIC SULFONAMIDES ARE CONTRAINDICATED IN INFANTS UNDER 2 MONTHS OF AGE except as adjunctive therapy with pyrimethamine in the treatment of congenital toxoplasmosis.

Usual Dosage for Infants over 2 Months of Age and Children

Initially, one-half the 24-hour dose. Maintenance, 150 mg/kg or 4 g/m^2, divided into 4 to 6 doses, every 24 hours, with a maximum of 6 g every 24 hours. Rheumatic fever prophylaxis, under 30 kg (66 pounds), 500 mg every 24 hours; over 30 kg (66 pounds), 1 g every 24 hours.

Usual Adult Dosage

Initially, 2 g to 4 g. Maintenance, 2 g to 4 g, divided into 3 to 6 doses, every 24 hours.

HOW SUPPLIED

sulfADIAZINE Tablets, USP for oral administration are available as 500 mg

White round bevel edged scored tablets, debossed with "CE"above "208"and bisect on the other side.

Bottle of 60 Tablets NDC 62135-842-60

Storage

Store at 20° to 25°C (68° to 77°F) [see USP Controlled Room Temperature].

Protect from moisture.

Dispense contents in a tight, light-resistant container as defined in the USP with a child-resistant closure, as required.

KEEP TIGHTLY CLOSED.

KEEP OUT OF THE REACH OF CHILDREN.

To report SUSPECTED ADVERSE REACTIONS, contact Chartwell RX, LLC at 1-845-232-1683 or FDA at 1-800-FDA-1088 or www.fda.gov/medwatch.

Manufactured for:

Chartwell RX, LLC

Congers, NY 10920

L72388

Rev. 09/2024

PRINCIPAL DISPLAY PANEL

Sulfadiazine Tablets, USP 500 mg - NDC 62135-842-60 - 60s Bottle Label